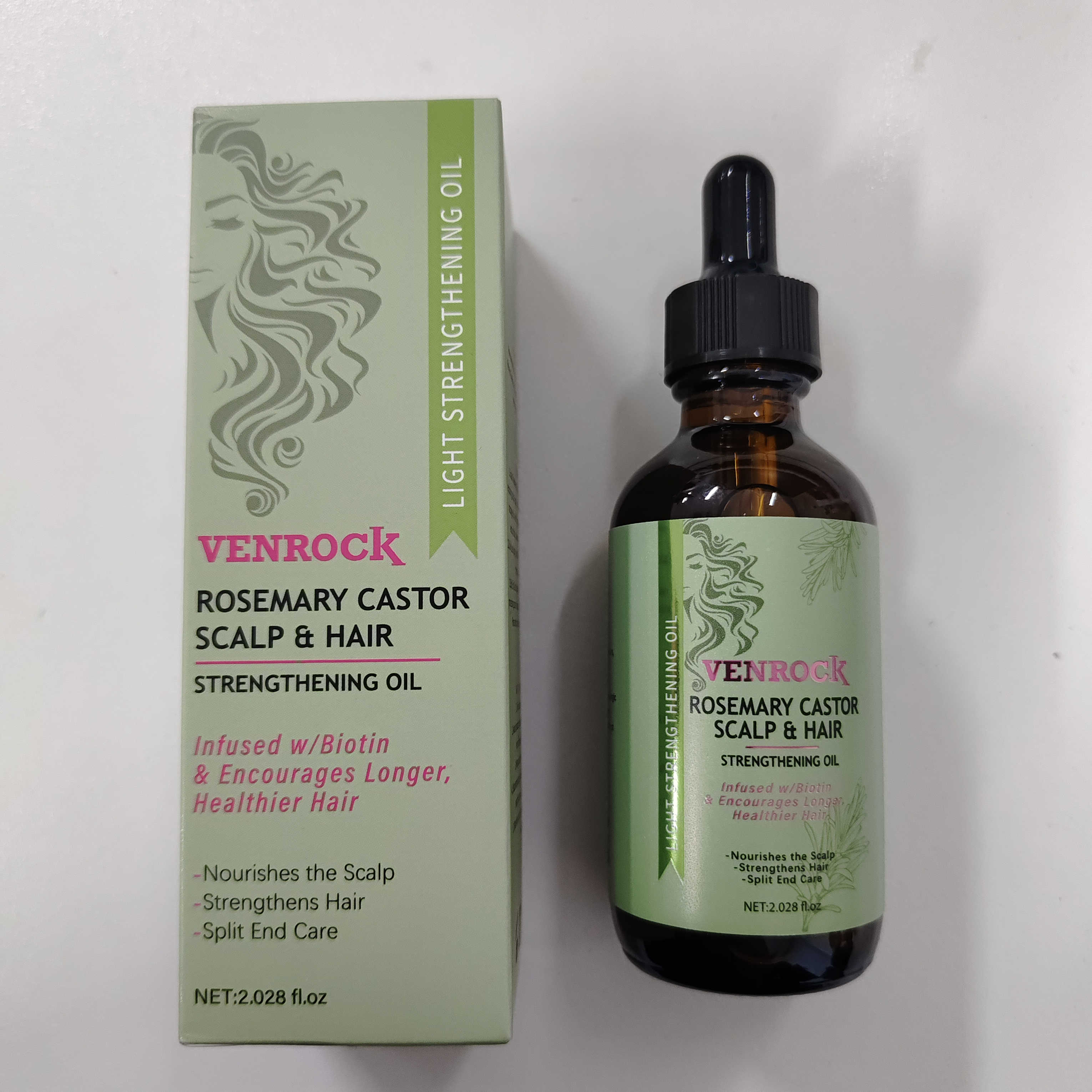 DRUG LABEL: VENROCK
NDC: 85772-0007 | Form: OIL
Manufacturer: Guangzhou Oupeng Cosmetics Co., Ltd
Category: otc | Type: HUMAN OTC DRUG LABEL
Date: 20251017

ACTIVE INGREDIENTS: ROSMARINUS OFFICINALIS (ROSEMARY) LEAF OIL 55 g/100 g; BIOTIN 0.001 g/100 g
INACTIVE INGREDIENTS: RICINUS COMMUNIS (CASTOR) SEED OIL 40 g/100 g; AMINO ACIDS, HAIR KERATIN 0.85 g/100 g; .ALPHA.-TOCOPHEROL ACETATE, D- 4.149 g/100 g

Active ingredient(s)

- Rosmarinus Officinalis (Rosemary) Leaf Oil 55%
- Biotin 0.001%

Purpose(s)

- Hair Strengthener
- Hair Strengthener

Uses

- Nourishes the Scalp
- Strengthens Hair
- Split End Care

Warnings

For external use only.

When using this product

Avoid contact with eyes. If contact occurs, rinse thoroughly with water.

Stop use and ask a doctor if

you experience any allergic reactions.

Keep out of reach of children.

In case of accidental ingestion, get medical help or contact a Poison Control Center right away.

Directions

- Scalp Treatment: Section hair into 4 parts exposing scalp. Apply a small amount of oil to scalp, massage oil in with fingers and comb through to ends of hair. Leave in and style as desired.
- Daily Use: Apply a small amount to scalp and comb through to ends.
- Split End Care: Apply oil to ends of hair, place a processing cap on head and leave on for 10 minutes. Rinse and proceed with shampooing.

Other information

Store in a cool, dry place away from direct sunlight.

Inactive ingredients

RICINUS COMMUNIS (CASTOR) SEED OIL,TOCOPHERYL ACETATE,KERATIN

Questions or comments?

934-935-7135 / Yiqinzhi726@gmail.com

PACKAGE LABEL

ROSEMARY CASTOR
SCALP & HAIR
STRENGTHENING OIL

Infused w/Biotin & Encourages Longer, Healthier Hair

-Nourishes the Scalp
-Strengthens Hair
-Split End Care

LIGHT STRENGTHENING OIL

NET:2.028 fl.oz